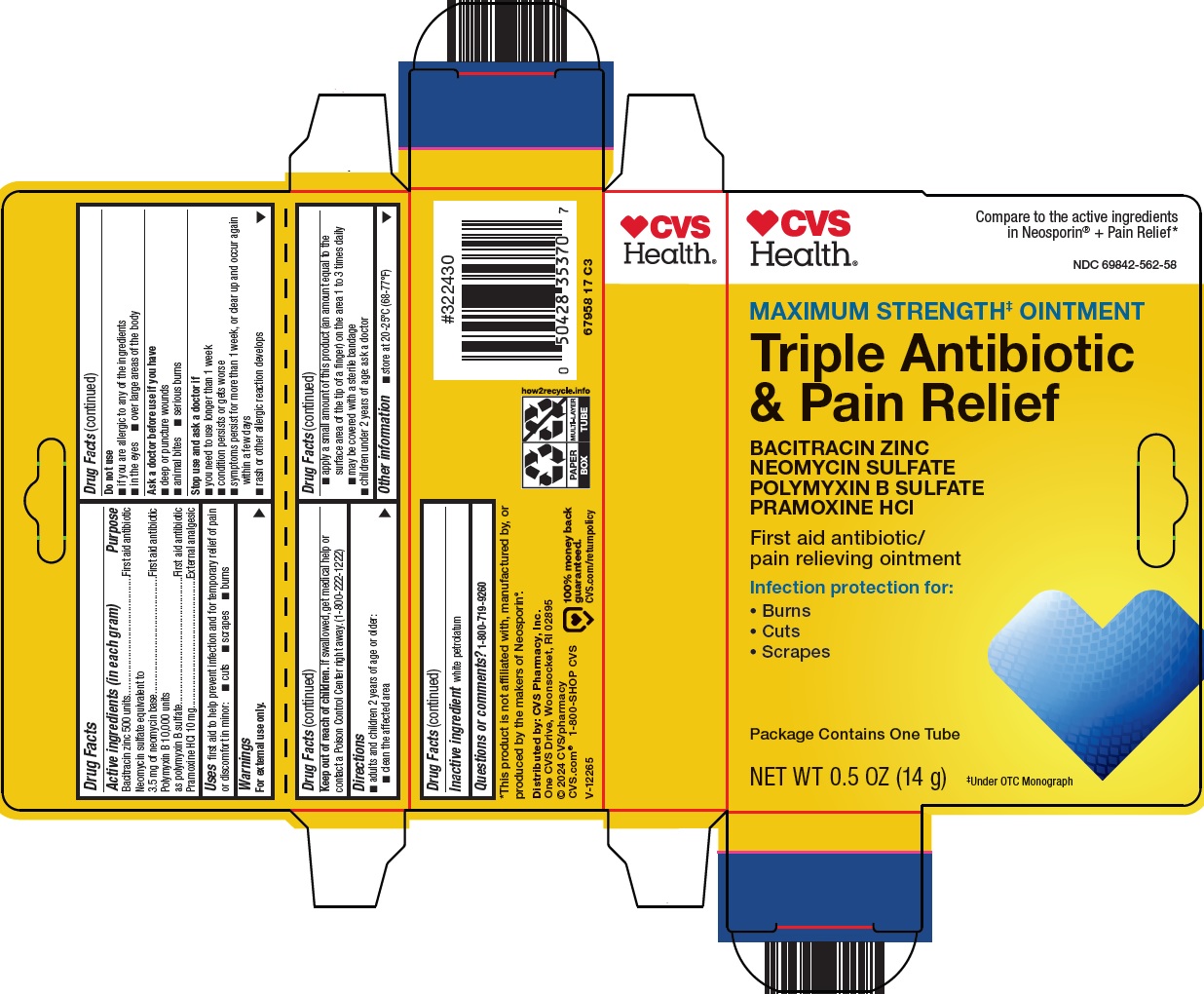 DRUG LABEL: triple antibiotic and pain relief
NDC: 69842-562 | Form: OINTMENT
Manufacturer: CVS Pharmacy
Category: otc | Type: HUMAN OTC DRUG LABEL
Date: 20241203

ACTIVE INGREDIENTS: BACITRACIN ZINC 500 [USP'U]/1 g; NEOMYCIN SULFATE 3.5 mg/1 g; POLYMYXIN B SULFATE 10000 [USP'U]/1 g; PRAMOXINE HYDROCHLORIDE 10 mg/1 g
INACTIVE INGREDIENTS: WHITE PETROLATUM

CVS Pharmacy, Inc. Triple Antibiotic & Pain Relief Drug Facts

Active ingredients (in each gram)

Bacitracin zinc 500 units

Neomycin sulfate equivalent to 3.5 mg of neomycin base

Polymyxin B 10,000 units as polymyxin B sulfate

Pramoxine HCl 10 mg

Purpose

First aid antibiotic

External analgesic

Uses

first aid to help prevent infection and for temporary relief of pain or discomfort in minor:

- cuts
- scrapes
- burns

Warnings

For external use only.

Do not use

- if you are allergic to any of the ingredients
- in the eyes
- over large areas of the body

Ask a doctor before use if you have

- deep or puncture wounds
- animal bites
- serious burns

Stop use and ask a doctor if

- you need to use longer than 1 week
- condition persists or gets worse
- symptoms persist for more than 1 week, or clear up and occur again within a few days
- rash or other allergic reaction develops

Keep out of reach of children.

If swallowed, get medical help or contact a Poison Control Center right away. (1-800-222-1222)

Directions

- adults and children 2 years of age or older:
  - clean the affected area
  - apply a small amount of this product (an amount equal to the surface area of the tip of a finger) on the area 1 to 3 times daily
  - may be covered with a sterile bandage
- children under 2 years of age: ask a doctor

Other information

- store at 20-25°C (68-77°F)

Inactive ingredients

white petrolatum

Principal Display Panel

CVS Health®

Compare to the active ingredients in Neosporin® + Pain Relief

MAXIMUM STRENGTH± OINTMENT

Triple Antibiotic & Pain Relief

BACITRACIN ZINC

NEOMYCIN SULFATE

POLYMYXIN B SULFATE

PRAMOXINE HCl

First aid antibiotic/pain relieving ointment

Infection protection for:

• Burns

• Cuts

• Scrapes

Packages Contains One Tube

NET WT 0.5 OZ (14 g)

±Under OTC Monograph